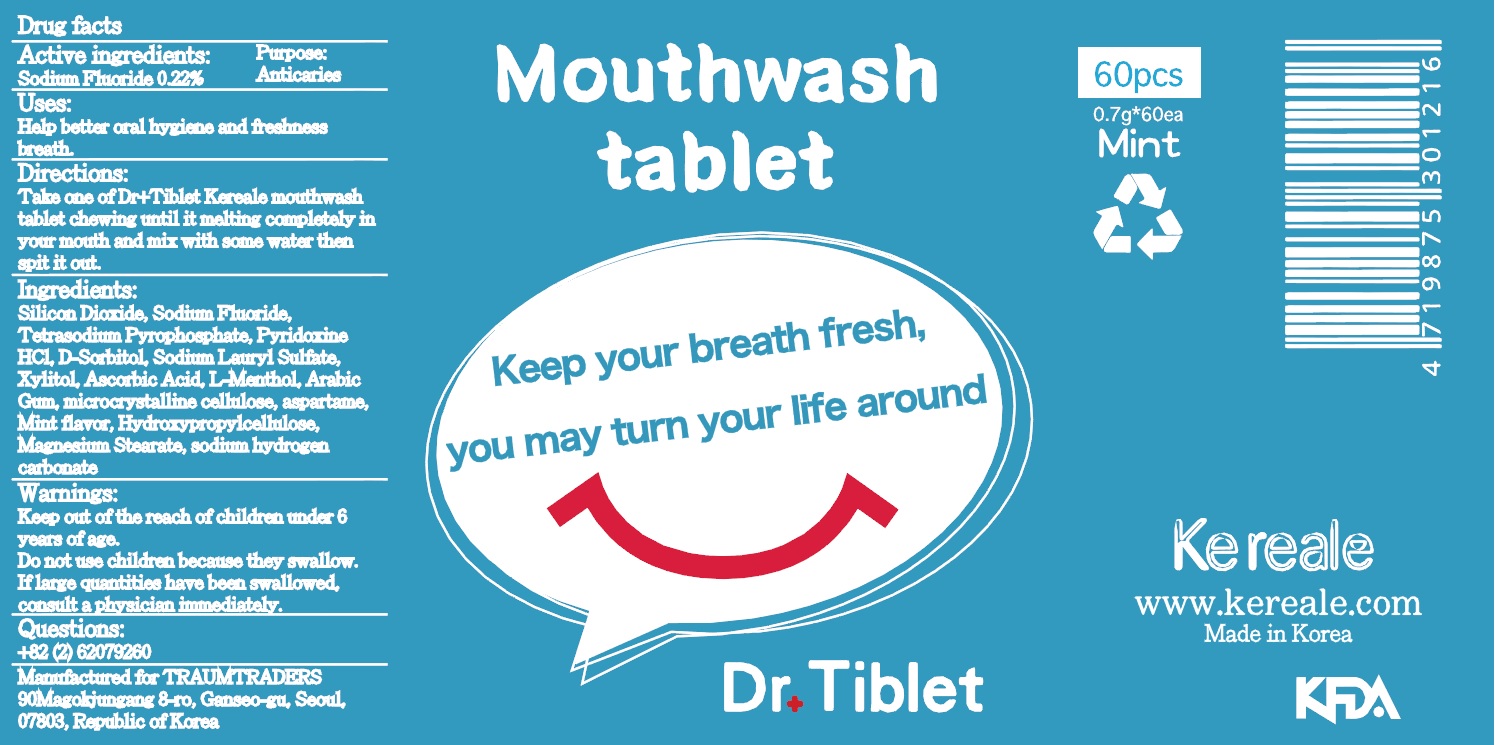 DRUG LABEL: DoctorTibletKereale
NDC: 72047-010 | Form: PASTE, DENTIFRICE
Manufacturer: TRAUM TRADERS
Category: otc | Type: HUMAN OTC DRUG LABEL
Date: 20180129

ACTIVE INGREDIENTS: Sodium Fluoride 0.001 g/0.7 g
INACTIVE INGREDIENTS: SODIUM LAURYL SULFATE; SILICON DIOXIDE

ACTIVE INGREDIENT

Active ingredients: Sodium Fluoride 0.22%

INACTIVE INGREDIENT

Inactive ingredients: D-Sorbitol, Sodium Lauryl Sulfate, Silicon Dioxide, Xylitol, microcrystalline cellulose, Mint Flavor, Magnesium Sterate, L-Menthol, Hydroxypropylellulose, Tetrasodium Pyrophosphate, sodium hydrogen carbonate, aspartame, Arabic Gum, Pyridoxine HCI, Ascorbic Acid

PURPOSE

Purpose: Anticaries

WARNINGS

Warnings: Keep out of the reach of children under 6 years of age. Do not use children because they may swallow. If large quantities have been swallowed, consult a physician immediately.

KEEP OUT OF REACH OF CHILDREN

Keep out of the reach of children under 6 years of age.

Uses

Uses: Help better oral hygiene and freshness breath.

Directions

Directions: Take one of Kereale mouth rinse tablet chewing until it melting completely in your mouth and mix with some water then spit it out.